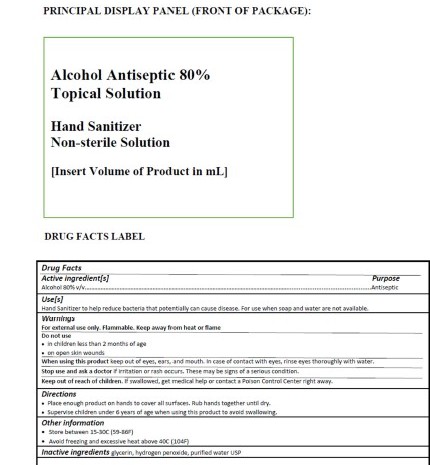 DRUG LABEL: Hand Sanitizer
NDC: 73912-100 | Form: LIQUID
Manufacturer: CJ Spirits LLC
Category: otc | Type: HUMAN OTC DRUG LABEL
Date: 20200813

ACTIVE INGREDIENTS: ALCOHOL 80 mL/100 mL
INACTIVE INGREDIENTS: HYDROGEN PEROXIDE 4.17 mL/100 mL; GLYCERIN 1.45 mL/100 mL; WATER 12.5 mL/100 mL

Active Ingredients

Alcohol 80%v/v

Do Not Use

In children less than two years of age or on open skin wounds

Warnings

For external use only. Flamable. Keep away from heat or flame

Stop Use

Stop use and ask doctor if irritation or rash occurs

Purpose

Antiseptic

Inactive Ingredients

glycerin, hydrogen peroxide, purified water USP

Instructions for use

Place enough product on your hand to cover all surfaces. Rub hands together until dry

Keep out of reach of children

If swallowed get medical help or contact a poison control center immediately

Other information

Store between 15-30C (59=86F)

Avoid freezing and excessive heat above 40C (104F)

Dosage & Administration

Place enough product on your hand to cover all surfaces. Rub hands together until dry.

Usage

Hand sanitizer to help reduce bacteria that can cause disease. For use when soap and water are not available

PACKAGE LABEL

Active Ingredients purpose

Alcohol 80%v/v...........................................................................antiseptic

Uses

Hand sanitizer to help reduce bacteria that can cause disease. For use when soap and water are not available

Warnings

For external use only. Flamable. Keep away from heat or flame

Do not use

In children less than two years of age

on open skin wounds

When using this product keep out of eyes, ears and mouth. In case of contact with eyes, rinse eyes thoroughly with water

Stop use and ask doctor if irritation or rash occurs

Keep out of reach of children.

If swallowed get medical help or contact a poison control center immediately

Place enough product on your hand to cover all surfaces. Rub hands together until dry.

Supervise children under 6 years of age when using this product to avoid swallowing.

Other information

Store between 15-30C (59=86F)

Avoid freezing and excessive heat above 40C (104F)

Inactive ingredients, glycerin, hydrogen peroxide, purified water USP